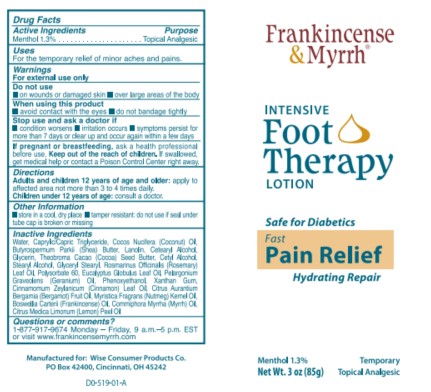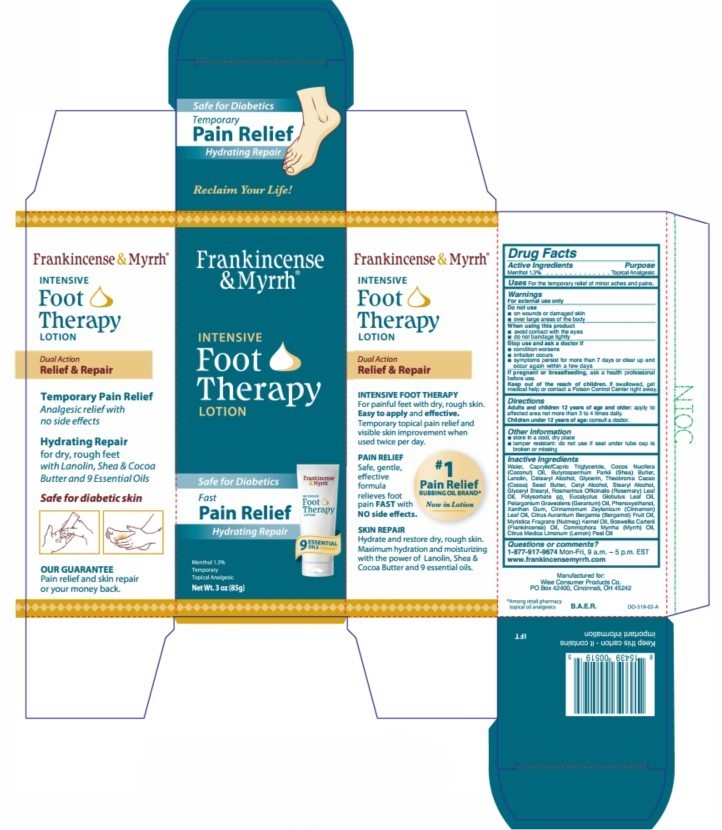 DRUG LABEL: Frankincense and Myrrh Intensive Foot Therapy
NDC: 42346-520 | Form: LOTION
Manufacturer: Wise Consumer Products
Category: otc | Type: HUMAN OTC DRUG LABEL
Date: 20251217

ACTIVE INGREDIENTS: MENTHOL 1.3 g/100 g
INACTIVE INGREDIENTS: WATER; MEDIUM-CHAIN TRIGLYCERIDES; GERANIUM OIL, ALGERIAN TYPE; NUTMEG OIL; STEARYL ALCOHOL; POLYSORBATE 60; EUCALYPTUS OIL; PHENOXYETHANOL; MYRRH OIL; LANOLIN; CETOSTEARYL ALCOHOL; GLYCERIN; COCOA BUTTER; GLYCERYL MONOSTEARATE; COCONUT OIL; BERGAMOT OIL; CETYL ALCOHOL; ROSEMARY OIL; XANTHAN GUM; CINNAMON OIL; FRANKINCENSE OIL; LEMON OIL, COLD PRESSED; SHEA BUTTER

Frankincense & Myrrh Intensive Foot Therapy Lotion

Active ingredient

Menthol 1.3%

Purpose

Menthol 1.3%................Topical Analgesic

Uses

For the temporary relief of minor aches and pains.

Warnings

For external use only

Do not use

- on wounds or damaged skin
- over large areas of the body

When using this product

- avoid contact with the eyes
- do not bandage tightly

Stop use and ask a doctor if

- condition worsens
- irritation occurs
- symptoms persist for more than 7 days or clear up and occur again within a few days

PREGNANCY OR BREAST FEEDING

If pregnant or breastfeeding, ask a health professional before use.

KEEP OUT OF REACH OF CHILDREN

Keep out of the reach of children. If swallowed, get medical help or contact a Poison Control Center right away.

Directions

Adults and children 12 years of age and older: apply to affected area not more than 3 to 4 times daily.

Children under 12 years of age: consult a doctor.

Other information

- store in a cool, dry place
- tamper resistant: do not use if seal under tube cap is broken or missing

Inactive ingredients

Water, Caprylic/Capric Triglyceride, Cocos Nucifera (Coconut) Oil, Butyrospermum Parkii (Shea) Butter, Lanolin, Cetearyl Alcohol, Glycerin, Theobroma Cacao (Cocoa) Seed Butter, Cetyl Alcohol, Stearyl Alcohol, Glyceryl Stearyl, Rosmarinus Officinalis (Rosemary) Leaf Oil, Polysorbate 60, Eucalyptus Globulus Leaf Oil, Pelargonium Graveolens (Geranium) Oil, Phenoxyethanol, Xanthan Gum, Cinnamomum Zeylanicum (Cinnamon) Leaf Oil, Citrus Aurantium Bergamia (Bergamot) Fruit Oil, Myristica Fragrans (Nutmeg) Kernel Oil, Boswellia Carterii (Frankincense) Oil, Commiphora Myrrha (Myrrh) Oil, Citrus Medica Limonum (Lemon) Peel Oil

Questions or comments?

1-877-917-9674 Mon-Fri, 9 a.m. - 5 p.m. EST

www.frankincensemyrrh.com

PACKAGE LABEL

Frankincense & Myrrh

Intensive

Foot

Therapy

Lotion

Safe for Diabetics

Fast

Pain Relief

Hydrating Repair

Menthol 1.3%

Temporary

Topical Analgesic

Net Wt. 3 oz (85g)